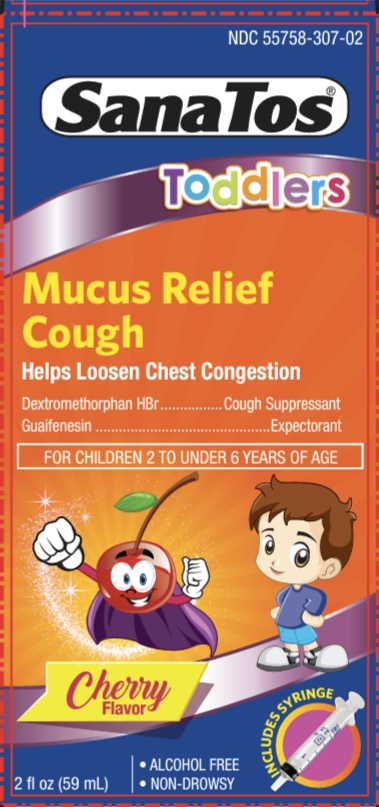 DRUG LABEL: SanaTos Mucus Relief Cold Toddlers
NDC: 55758-307 | Form: LIQUID
Manufacturer: Pharmadel LLC
Category: otc | Type: HUMAN OTC DRUG LABEL
Date: 20250204

ACTIVE INGREDIENTS: GUAIFENESIN 50 mg/2.5 mL; DEXTROMETHORPHAN HYDROBROMIDE 2.5 mg/2.5 mL
INACTIVE INGREDIENTS: SORBITOL SOLUTION; SODIUM BENZOATE; ANHYDROUS CITRIC ACID; GLYCERIN; PROPYLENE GLYCOL; WATER; D&C RED NO. 33; FD&C RED NO. 40; XANTHAN GUM; SUCRALOSE

Santos Toddler Mucus (AP/ PLE)

Active Ingredients & Purposes

PURPOSE

Active ingredients (in each 2.5 mL) | Purposes
Dextromethorphan HBr 2.5 mg ..... | Cough suppressant
Guaifenesin 50 mg............ | Expectorant

Uses

- temporarily relieves cough due to minor throat and bronchial irritation as may occur with a cold
- helps loosen phlegm (mucus) and thin bronchial secretions to drain the bronchial tubes

Warnings

Do not use

in a child who is taking a prescription monoamine oxidase inhibitor (MAOI) (certain drugs for depression, psychiatric, or emotional conditions, or Parkinson’s disease), or for 2 weeks after stopping the MAOI drug. If you do not know if your child’s prescription drug contains an MAOI, ask a doctor or pharmacist before giving this product.

Ask a doctor before use if the child has a

- cough that is accompanied by excessive phlegm (mucus)
- persistent or chronic cough such as occurs with asthma

When using this product

do not use more than directed

Stop use and ask a doctor, if the child has a

cough that persists for more than 7 days, tends to recur, or is accompanied by fever, rash, or persistent headache. A persistent cough may be a sign of a serious condition.

Keep out of reach of children.

In case of overdose, get medical help or contact a Poison Control Center right away.

Directions

- do not give a child more than 6 doses in 24 hour period
- repeat the dose every 4 hours
- use only included oral syringe to measure dose

Age | Dose
children 2 to under 6 years of age | 2.5 mL every 4 hours
children under 2 years of age | consult a doctor

Other information

■ store between 68-77°F (20-25°C)

■ do not refrigerate

■ keep carton for full direction for use

Inactive ingredients

anhydrous citric acid, D&C red #33, FD&C red #40, flavor, glycerin, propylene glycol, sodium benzoate, sorbitol solution, sucralose, xanthan gum, water

Questions?

+1-866-359-3478 (M-F) 9 AM to 5 PM EST or www.pharmadel.com

Distributed by / Distribuido por:

PHARMADEL LLC

New Castle, DE 19720